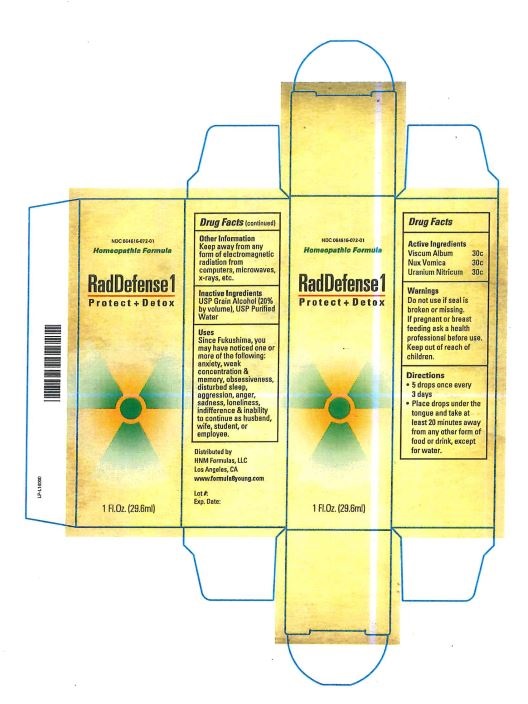 DRUG LABEL: RadDefense1
NDC: 64616-118 | Form: LIQUID
Manufacturer: Vitality Works, Inc.
Category: homeopathic | Type: HUMAN OTC DRUG LABEL
Date: 20251217

ACTIVE INGREDIENTS: URANYL NITRATE HEXAHYDRATE 30 [hp_C]/29.6 mL; STRYCHNOS NUX-VOMICA SEED 30 [hp_C]/29.6 mL; VISCUM ALBUM WHOLE 30 [hp_C]/29.6 mL
INACTIVE INGREDIENTS: WATER; ALCOHOL

RadDefense1

Active Ingredients

Viscum Album 30C

Nux Vomica 30C

Uranium Nitricum 30C

Inactive Ingredients

USp Grain Alcohol (20% by volume), USP Purified water

Uses

Since Fukushima you may have noticed one or more of the following: anxiety, weak concentration & memory, obsessiveness, disturbed sleep, aggression, anger, sadness, loneliness, indifference & ability to continue as husband, wife, student, or employee

Directions

5 drops once every 3 days

Place drops under the tongue and take at least 20 minutes away from any other form of fodd or drink, excpet water

Warnings

Do not use if seal is broken or missing.

If pregnant or breastfeeding, ask a health care professional before use.

Keep out of reach of children.

Other information

Keep away from any form of electromagnetic radiation from computers, microwaves, x-rays, etc.

Distributed By

HNM Formulas, LLC

825 Wilshire Blvd., #110

Santa Monica, CA 90401

www.formula8young.com

Warnings

Keep out of reach of children.

Uses

Since Fukushima, you may have noticed one or more of the following: anxiety, weak concentration & memory, obsessiveness, disturbed sleep, aggression, anger, sadness, indifference & inability to continue as husband, wife, student, or employee